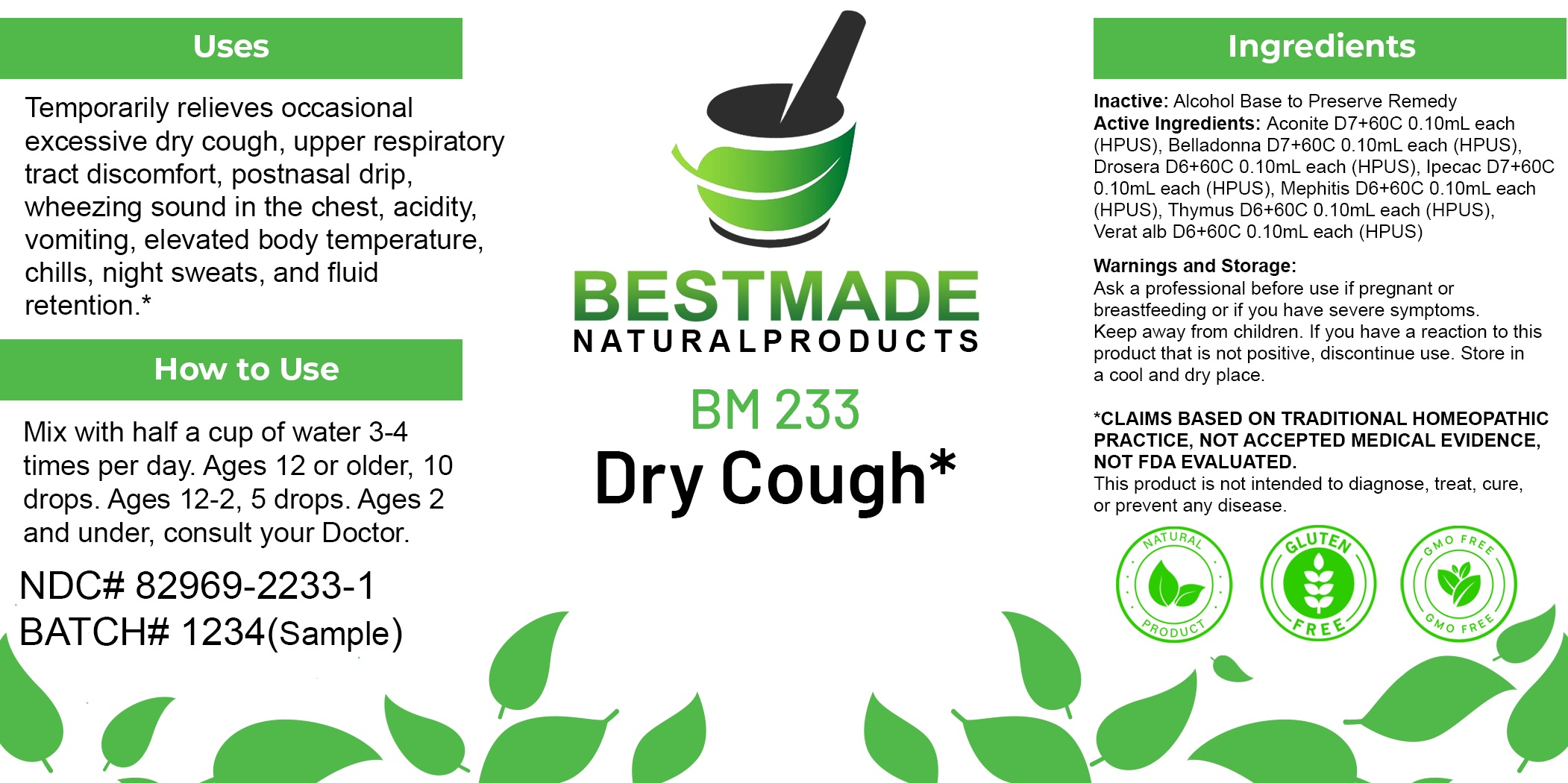 DRUG LABEL: Bestmade Natural Products BM233
NDC: 82969-2233 | Form: LIQUID
Manufacturer: Bestmade Natural Products
Category: homeopathic | Type: HUMAN OTC DRUG LABEL
Date: 20250304

ACTIVE INGREDIENTS: DROSERA ROTUNDIFOLIA 30 [hp_C]/30 [hp_C]; ACONITUM NAPELLUS 30 [hp_C]/30 [hp_C]; ATROPA BELLADONNA 30 [hp_C]/30 [hp_C]; VERATRUM ALBUM ROOT 30 [hp_C]/30 [hp_C]; THYMUS SERPYLLUM 30 [hp_C]/30 [hp_C]; MEPHITIS MEPHITIS ANAL GLAND FLUID 30 [hp_C]/30 [hp_C]; IPECAC 30 [hp_C]/30 [hp_C]
INACTIVE INGREDIENTS: ALCOHOL 30 [hp_C]/30 [hp_C]

BM233

DOSAGE AND ADMINISTRATION

How to Use

Mix with half a cup of water 3-4 times per day. Ages 12 or older, 10 drops. Ages 12-2, 5 drops. Ages 2 and under, consult your Doctor.

Inactive:

Alcohol Base to Preserve Product

ACTIVE INGREDIENT

Active Ingredients: Aconite D7+60C 0.10mL each (HPUS), Belladonna D7+60C 0.10mL each (HPUS), Drosera D6+60C 0.10mL each (HPUS), Ipecac D7+60C 0.10mL each (HPUS), Mephitis D6+60C 0.10mL each (HPUS), Thymus D6+60C 0.10mL each (HPUS), Verat alb D6+60C 0.10mL each (HPUS)

KEEP OUT OF REACH OF CHILDREN

Warnings and Storage:

Ask a professional before use if pregnant or breastfeeding or if you have severe symptoms.

Keep away from children. If you have a reaction to this product that is not positive, discontinue use. Store in a cool and dry place

*CLAIMS BASED ON TRADITIONAL HOMEOPATHIC PRACTICE, NOT ACCEPTED MEDICAL EVIDENCE NOT FDA EVALUATED.
This product is not intended to diagnose, treat, cure, or prevent any disease.

Warnings and Storage:

Ask a professional before use if pregnant or breastfeeding or if you have severe symptoms.

Keep away from children. If you have a reaction to this product that is not positive, discontinue use. Store in a cool and dry place

*CLAIMS BASED ON TRADITIONAL HOMEOPATHIC PRACTICE, NOT ACCEPTED MEDICAL EVIDENCE NOT FDA EVALUATED.
This product is not intended to diagnose, treat, cure, or prevent any disease.

Uses
Temporarily relieves occasional excessive dry cough, upper respiratory tract discomfort, postnasal drip, wheezing sound in the chest, acidity, vomiting, elevated body temperature chills, night sweats, and fluid retention.*

Uses
Temporarily relieves occasional excessive dry cough, upper respiratory tract discomfort, postnasal drip, wheezing sound in the chest, acidity, vomiting, elevated body temperature chills, night sweats, and fluid retention.*

Entire package label